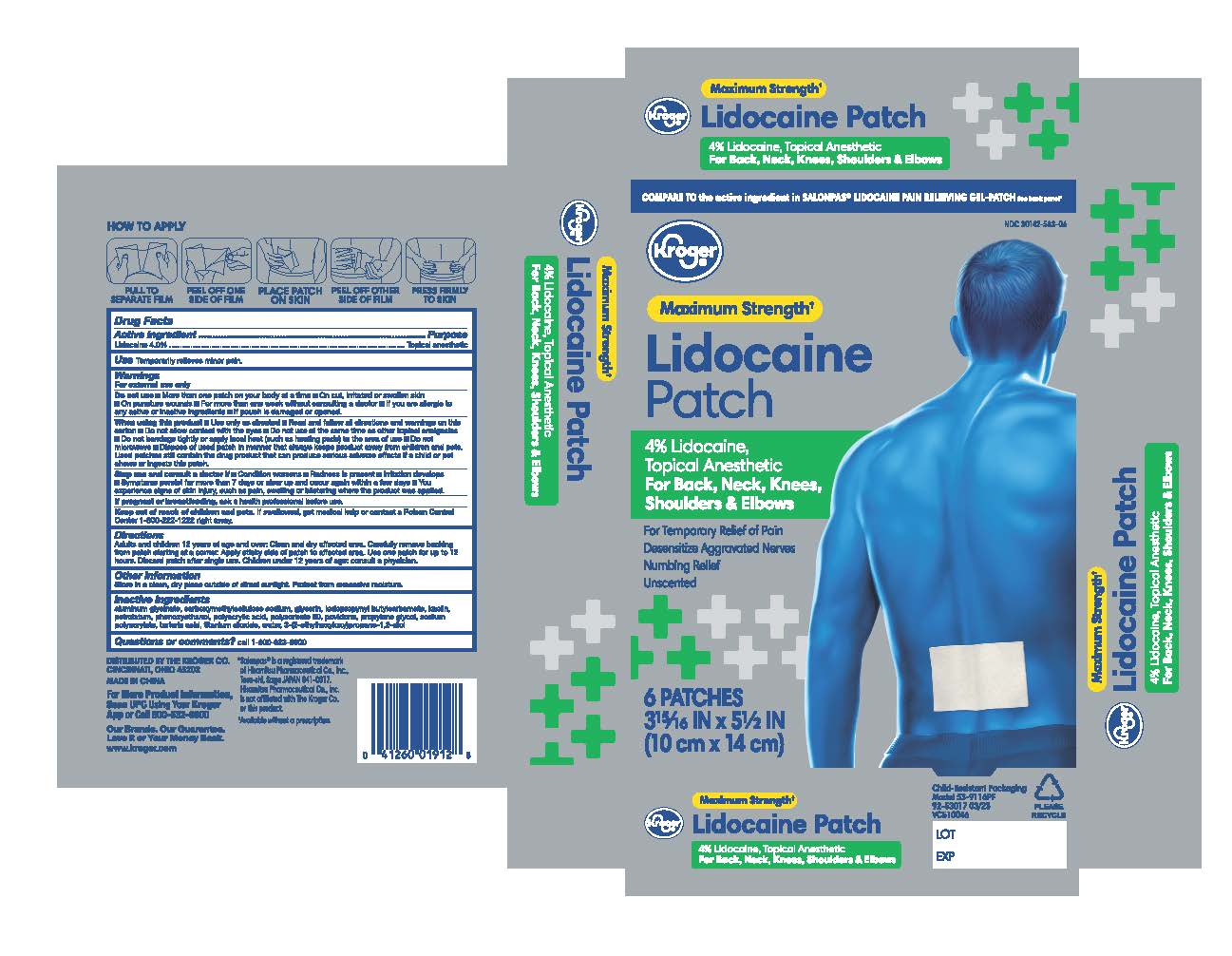 DRUG LABEL: Kroger Pain Relief Lidocaine Patch
NDC: 30142-583 | Form: PATCH
Manufacturer: Kroger Company
Category: otc | Type: HUMAN OTC DRUG LABEL
Date: 20251230

ACTIVE INGREDIENTS: LIDOCAINE 4 g/100 g
INACTIVE INGREDIENTS: KAOLIN; POLYSORBATE 80; PROPYLENE GLYCOL; DIHYDROXYALUMINUM AMINOACETATE; TITANIUM DIOXIDE; CARBOXYMETHYLCELLULOSE SODIUM; ETHYLHEXYLGLYCERIN; POLYACRYLIC ACID (8000 MW); PETROLATUM; GLYCERIN; SODIUM POLYACRYLATE (8000 MW); TARTARIC ACID; POVIDONE, UNSPECIFIED; PHENOXYETHANOL; IODOPROPYNYL BUTYLCARBAMATE; WATER

Kroger Pain Relief 4% Lidocaine Patch

Active Ingredient

Lidocaine 4%

Purpose

Topical anesthetic

Use

Temporary relieves minor pain

Warnings

For external use only

Do not Use

1. more than 1 patch on your body at a time

2. on cut, irritated or swollen skin

3. On puncture wounds

4. For more than one week without consulting a doctor

5. If you are allergic to any active or inactive ingredients

if pouch is damaged or opened

When using this product

1. Use only as directed

2. Read and follow all directions and warnings on this carton

3. Do not allow contact with the eyes

4. Do not use at the same time as other topical analgesics

5. Do not bandage tightly or apply local heat (such as heating pads) to the area of use

6. Do not microwave

7. Dispose of used patch in manner that always keeps product away from children or pets. Used patches still contain the drug product that can produce serious adverse effects if a child or pet chews or ingests this patch.

Stop use and consult a doctor

1. condition worsens

2. redness is present

3. irritation develops

4. symptoms persist for more than 7 days or clear up and occur again within a few days

5. you experience signs of skin injury, such as pain, swelling, or blistering where the product was applied

If pregnant or breastfeeding

ask a health professional before use

Keep out of reach of children and pets

If swallowed, get medical help or contact a Poison Control Center 1-800-222-1222 right away

Directions

1. clean and dry affected area

2. carefully remove backing from patch starting at the corner

3. Apply sticky side of patch to affected area.

4. Use one patch for up to 12 hours.

5. Discard patch after single use

children under 12 years or age: consult a physician

Other Information

Store in a clean, dry place outside of direct sunlight. Protect from excessive moisture

Inactive Ingredients

aluminum glycinate, carboxymethylcellulose sodium, glycerin, iodopropynyl butylcarbamate, kaolin, petrolatum, phenoxyethanol, polyacrylic acid, polysorbate 80, povidone, propylene glycol, sodium polyacrylate, tartaric acid, titanium dioxide, water, 3-(2-ethylhexyloxy)propane-1,2-diol